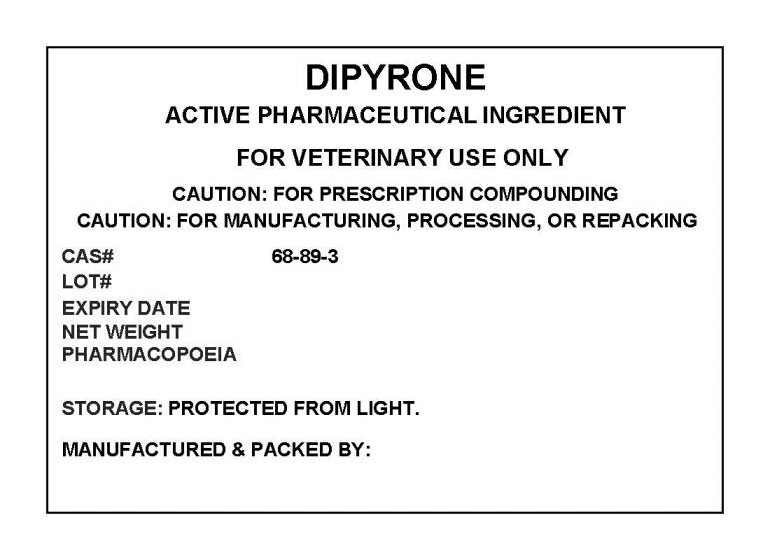 DRUG LABEL: METAMIZOLE SODIUM
NDC: 72969-022 | Form: POWDER
Manufacturer: PROFESSIONAL GROUP OF PHARMACISTS NEW YORK LLC
Category: other | Type: BULK INGREDIENT
Date: 20190314

ACTIVE INGREDIENTS: METAMIZOLE SODIUM 1 g/1 g

METAMIZOLE SODIUM

PACKAGE LABEL

dipyronelabel.jpg